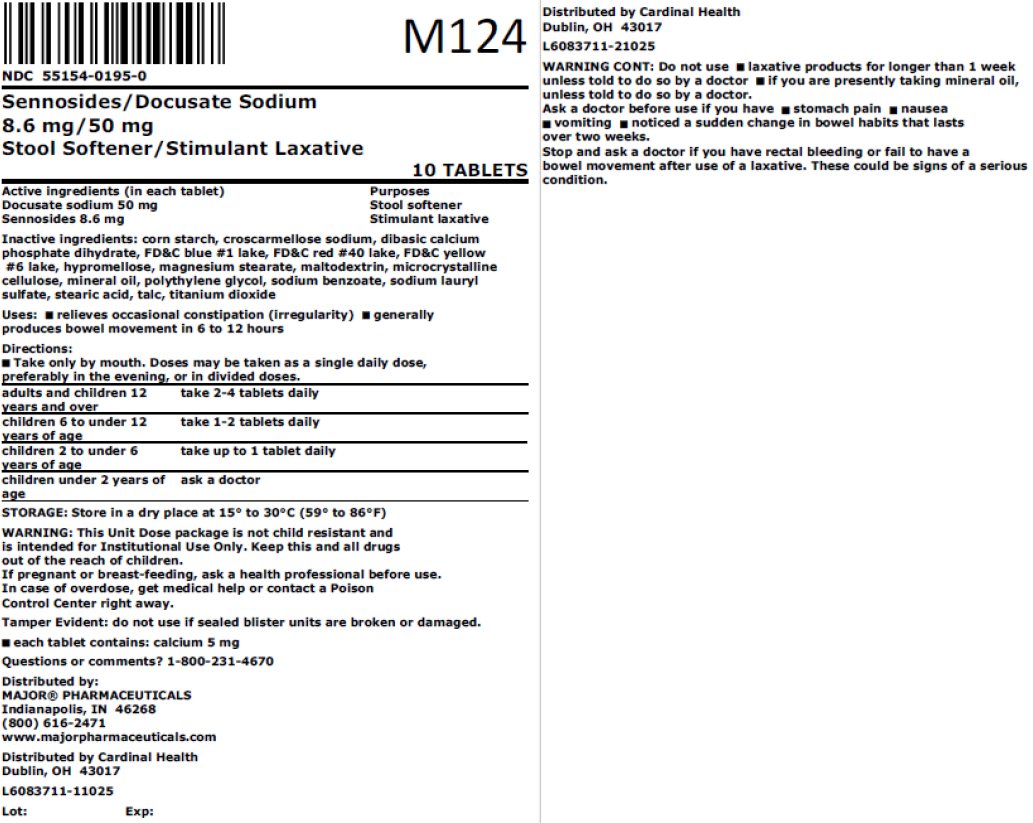 DRUG LABEL: Sennosides, Docusate Sodium
NDC: 55154-0195 | Form: TABLET, FILM COATED
Manufacturer: Cardinal Health 107, LLC
Category: otc | Type: HUMAN OTC DRUG LABEL
Date: 20251112

ACTIVE INGREDIENTS: DOCUSATE SODIUM 50 mg/1 1; SENNOSIDES 8.6 mg/1 1
INACTIVE INGREDIENTS: STARCH, CORN; CROSCARMELLOSE SODIUM; DIBASIC CALCIUM PHOSPHATE DIHYDRATE; FD&C BLUE NO. 1 ALUMINUM LAKE; FD&C RED NO. 40 ALUMINUM LAKE; FD&C YELLOW NO. 6 ALUMINUM LAKE; HYPROMELLOSE, UNSPECIFIED; MAGNESIUM STEARATE; MALTODEXTRIN; MICROCRYSTALLINE CELLULOSE; LIGHT MINERAL OIL; POLYETHYLENE GLYCOL 400; SODIUM BENZOATE; SODIUM LAURYL SULFATE; STEARIC ACID; TALC; TITANIUM DIOXIDE

Sennosides / Docusate Sodium

Drug Facts

Active ingredients (in each tablet)

Docusate sodium 50 mg
Sennosides 8.6 mg

Purposes

Stool softener
Stimulant laxative

Uses

- relieves occasional constipation (irregularity)
- generally produces bowel movement in 6 to 12 hours

Warnings

.

Do not use

- laxative products for longer than 1 week unless told to do so by a doctor
- if you are presently taking mineral oil, unless told to do so by a doctor

Ask a doctor before use if you have

- stomach pain
- nausea
- vomiting
- noticed a sudden change in bowel habits that lasts over two weeks

Stop use and ask a doctor if

you have rectal bleeding or fail to have a bowel movement after use of a laxative. These could be signs of a serious condition.

If pregnant or breast-feeding,

ask a health professional before use.

Keep out of reach of children.

In case of overdose, get medical help or contact a Poison Control Center right away.

Directions

- take only by mouth. Doses may be taken as a single daily dose, preferably in the evening, or in divided doses.

adults and children 12 years and over | take 2-4 tablets daily
children 6 to under 12 years of age | take 1-2 tablets daily
children 2 to under 6 years of age | take up to 1 tablet daily
children under 2 years | ask a doctor

Other information

- each tablet contains: calcium 5 mg
- Store in a dry place at 15° – 30°C (59° – 86°F).

Inactive Ingredients

corn starch, croscarmellose sodium, dibasic calcium phosphate dihydrate, FD&C blue #1 lake, FD&C red #40 lake, FD&C yellow #6 lake, hypromellose, magnesium stearate, maltodextrin, microcrystalline cellulose, mineral oil, polyethylene glycol, sodium benzoate, sodium lauryl sulfate, stearic acid, talc, titanium dioxide.

Questions or comments?

1-800-231-4670

Keep this carton for complete product information

Tamper Evident:

Do not use if sealed blister units are broken or damaged.

Distributed by:
MAJOR® PHARMACEUTICALS
Indianapolis, IN 46268
(800) 616-2471
www.majorpharmaceuticals.com

Overbagged with 10 tablets per bag, NDC 55154-0195-0

WARNING: This Unit Dose package is not child resistant and is Intended for Institutional Use Only. Keep this and all drugs out of the reach of children.

Distributed By:

Cardinal Health

Dublin, OH 43017

L6083711-11025 / L6083711-21025

Rev. 02/24 | M-29 | Re-order No. 701390

Principal Display Panel

NDC 55154-0195-0

Sennosides/Docusate Sodium

8.6 mg/50 mg

Stool Softener/Stimulant Laxative

10 TABLETS